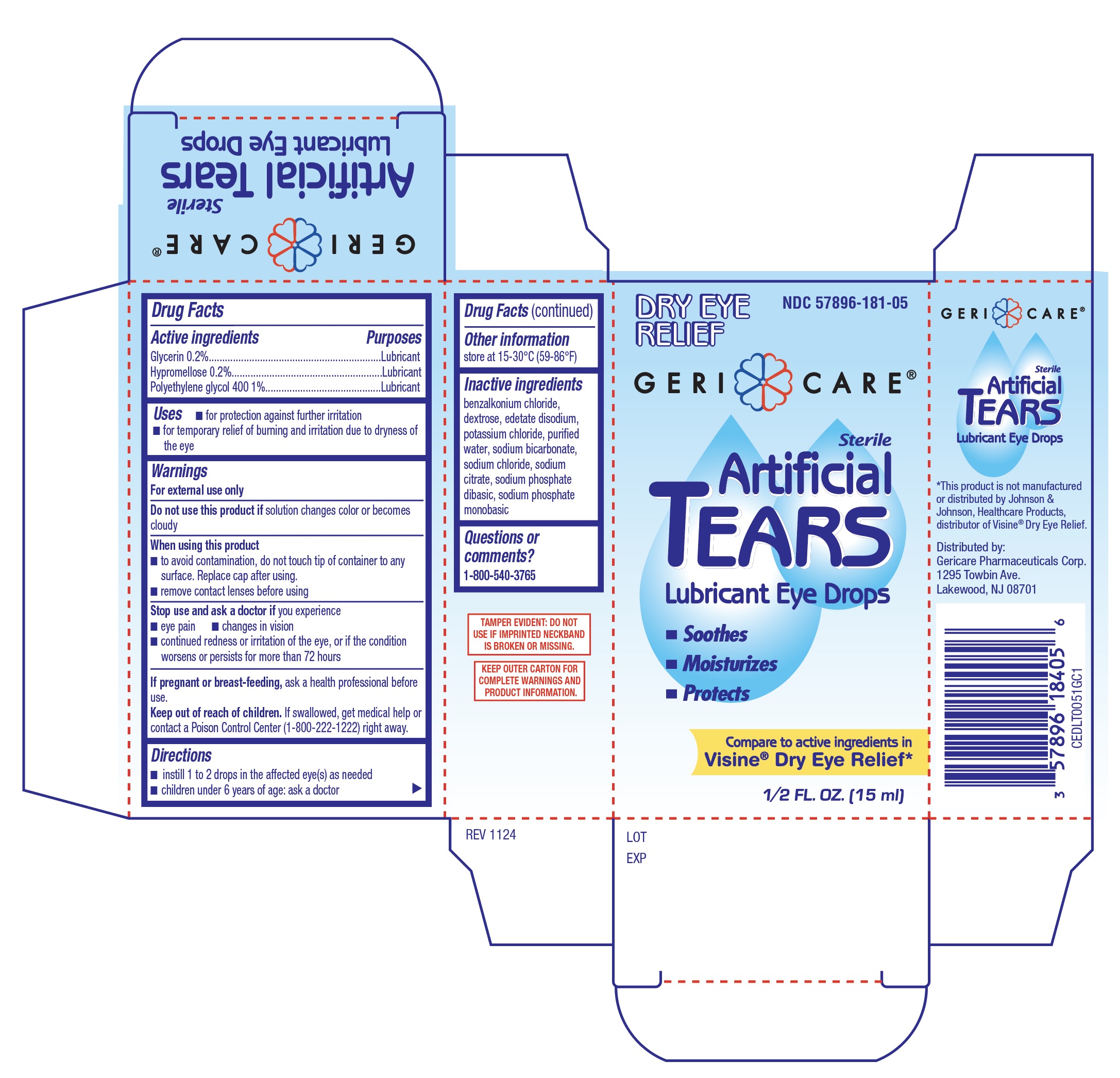 DRUG LABEL: Artificial Tears
NDC: 57896-181 | Form: SOLUTION/ DROPS
Manufacturer: Geri-Care Pharmaceuticals, Corp
Category: otc | Type: HUMAN OTC DRUG LABEL
Date: 20251219

ACTIVE INGREDIENTS: GLYCERIN 0.002 mg/1 mg; HYPROMELLOSES 0.002 mg/1 mg; POLYETHYLENE GLYCOL 400 0.01 mg/1 mg
INACTIVE INGREDIENTS: DEXTROSE; SODIUM PHOSPHATE, DIBASIC, DIHYDRATE; SODIUM BICARBONATE; EDETATE DISODIUM; BENZALKONIUM CHLORIDE; SODIUM PHOSPHATE, MONOBASIC; POTASSIUM CHLORIDE; WATER; SODIUM CHLORIDE; SODIUM CITRATE

GeriCare Artificial Tears Lubricant Eye Drops 15mL (PLD)

Active ingredients

Glycerin 0.2%

Hypromellose 0.2%

Polyethylene glycol 400 1%

Purpose

Lubricant

Uses

- for protection against further irritation
- for temporary relief of burning and irritation due to dryness of the eye

Warnings

For external use only

Do not use this product if

solution changes color or becomes cloudy

When using this product

- to avoid contamination, do not touch tip of container to any surface. Replace cap after using.
- remove contact lenses before using

Stop use and ask a doctor if

you experience

- eye pain
- changes in vision
- continued redness or irritation of the eye, or if the condition worsens or persists for more than 72 hours

If pregnant or breast-feeding,

ask a health professional before use.

Keep out of reach of children.

If swallowed, get medical help or contact a Poison Control Center (1-800-222-1222) right away.

Directions

- instill 1 or 2 drops in the affected eye(s) as needed
- children under 6 years of age: ask a doctor

Other information

- store at 15°-30°C (59°-86°F)

Inactive ingredients

benzalkonium chloride, dextrose, edetate disodium, potassium chloride, purified water, sodium bicarbonate, sodium chloride, sodium citrate, sodium phosphate dibasic, sodium phosphate monobasic

Questions or comments?

1-800-540-3765